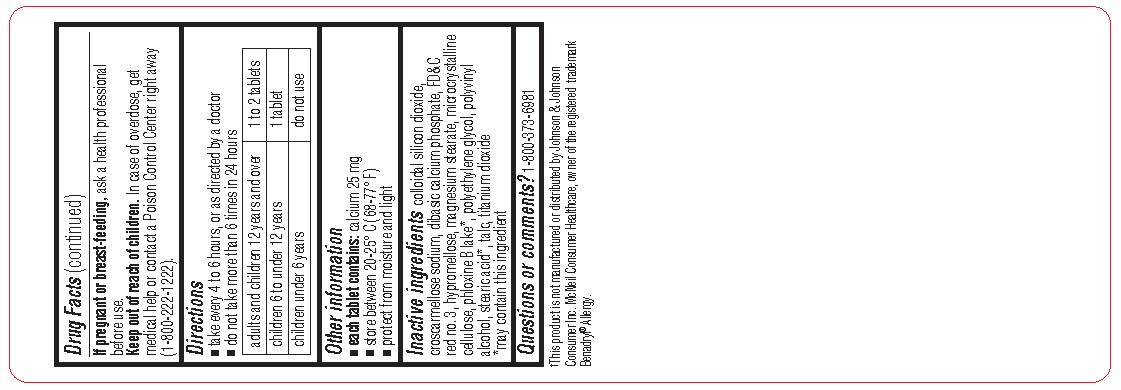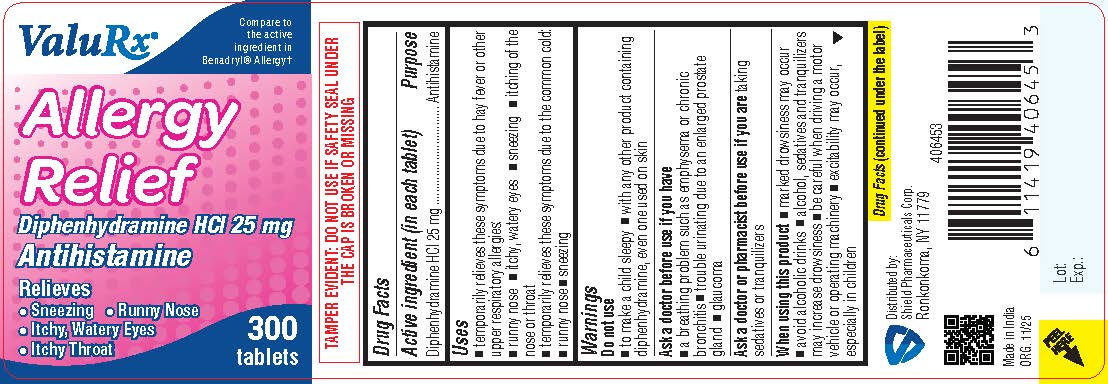 DRUG LABEL: Allergy Relief
NDC: 83059-0117 | Form: TABLET, COATED
Manufacturer: Shield Pharmaceuticals Corp
Category: otc | Type: HUMAN OTC DRUG LABEL
Date: 20251209

ACTIVE INGREDIENTS: DIPHENHYDRAMINE HYDROCHLORIDE 25 mg/1 1
INACTIVE INGREDIENTS: MAGNESIUM STEARATE; MICROCRYSTALLINE CELLULOSE; POLYETHYLENE GLYCOL, UNSPECIFIED; PHLOXINE; POLYVINYL ALCOHOL; STEARIC ACID; TALC; TITANIUM DIOXIDE; DIBASIC CALCIUM PHOSPHATE DIHYDRATE; SILICON DIOXIDE; CROSCARMELLOSE SODIUM; FD&C RED NO. 3; HYPROMELLOSES

Allergy Relief

Drug Facts

Active ingredient (in each tablet)

Diphenhydramine HCl 25 mg

Purpose

Antihistamine

Uses

- temporarily relieves these symptoms due to hay fever or other upper respiratory allergies:
- runny nose
- itchy, watery eyes
- sneezing
- itching of the nose or throat
- temporarily relieves these symptoms due to the common cold:
- runny nose
- sneezing

Do not use

- to make a child sleepy
- with any other product containing diphenhydramine, even one used on skin

Ask a doctor before use if you have

- a breathing problem such as emphysema or chronic bronchitis
- trouble urinating due to an enlarged prostate gland
- glaucoma

Ask a doctor or pharmacist before useif you are taking sedatives or tranquilizers

When using this product

- marked drowsiness may occur
- avoid alcoholic drinks
- alcohol, sedatives and tranquilizers may increase drowsiness
- be careful when driving a motor vehicle or operating machinery
- excitability may occur, especially in children

PREGNANCY OR BREAST FEEDING

If pregnant or breast-feeding,ask a health professional before use.

Keep out of reach of children. In case of overdose, get medical help or contact a Poison Control Center (1-800-222-1222) right away.

Directions

- take every 4 to 6 hours, or as directed by a doctor
- do not take more than 6 times in 24 hours

adults and children 12 years and over | 1 to 2 tablets
children 6 to under 12 years | 1 tablet
children under 6 years | do not use

Other information

- each tablet contains:calcium 25 mg
- store between 20-25° C (68-77° F)
- protect from moisture and light

Inactive ingredients

colloidal silicon dioxide, croscarmellose sodium, dibasic calcium phosphate, FD&C red no. 3, hypromellose, magnesium stearate, microcrystalline cellulose, phloxine B lake*, polyethylene glycol, polyvinyl alcohol, stearic acid*, talc, titanium dioxide

*may contain this ingredient

Questions or comments?

1-800-373-6981

Distributed by:
Shield Pharmaceuticals Corp.
Ronkonkoma, NY 11779

PRINCIPAL DISPLAY PANEL

Allergy Relief

Diphenhydramine HCl 25 mg

Label